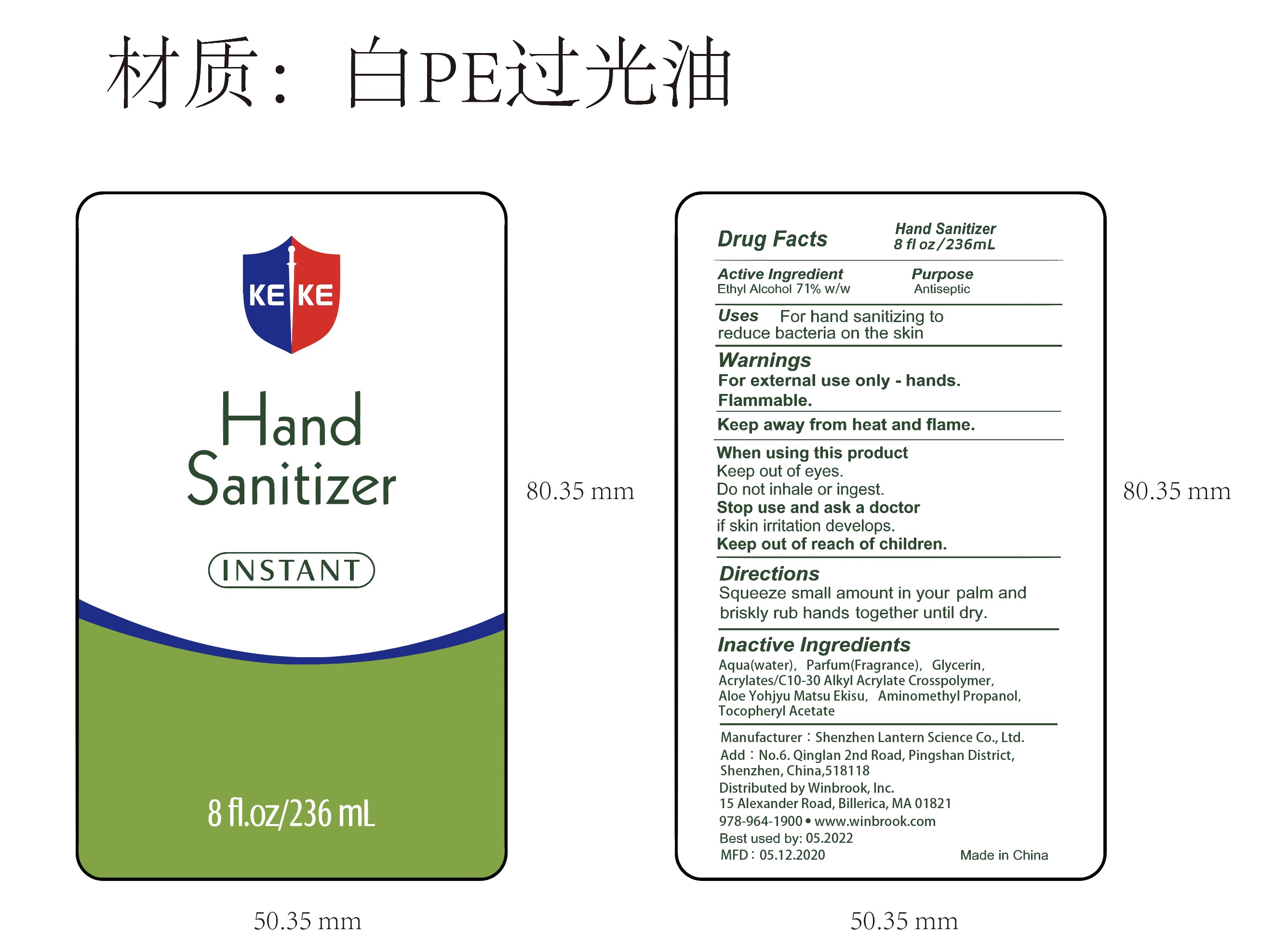 DRUG LABEL: KEKE hand sanitizer 236ml
NDC: 54860-280 | Form: LIQUID
Manufacturer: Shenzhen Lantern Scicence Co.,Ltd.
Category: otc | Type: HUMAN OTC DRUG LABEL
Date: 20200525

ACTIVE INGREDIENTS: ALCOHOL 71 g/100 g
INACTIVE INGREDIENTS: ALOE ANDONGENSIS WHOLE 0.1 g/100 g; ALOE 0.15 g/100 g; CARBOMER INTERPOLYMER TYPE A (55000 CPS) 0.26 g/100 g; AMINOMETHYLPROPANOL 0.08 g/100 g; WATER 27.9 g/100 g; GLYCERIN 0.5 g/100 g; .ALPHA.-TOCOPHEROL ACETATE 0.01 g/100 g

KEKE hand sanitizer 236ml

Active Ingredient

Active Ingredient Purpose

Ethyl Alcohol 71%（w/w） Antiseptic

USE

For hand sanitizing to reduce bacteria on the skin.

DOSAGE AND ADMINISTRATION

Recommended for repeated use.

use anywhere without water.

Warnings

For external use only-hands.

Flammable,keep away from heat and flame.

WARNINGS AND PRECAUTIONS

For external use only.

Flammable, keep away from heat and flame.

STOP USE

Discontinue if skin becomes irritated and ask a doctor .

Keep out of reach of children. In case of accidental ingestion, seek professional assistance or contact a poson control center immediately.

Inactive ingredients

Water, Parfum(Fragrance),Glycerin,Acrylates/C10-30 Alkyl Acrylate Crosspolymer,Aloe Yohjyu Matsu Ekisu,Aminomethyl Propanol,Tocopheryl Acetate.

Directions

squeeze small amount in your palm and briskly rub hands together until dry.

When using this product

keep out of eyes. In case of contact with eyes, flush thoroughly with water.

Do not inhale or ingest.

Avoid contact with broken skin.

Other information

Do not store above 105F.

May discolor some fabrics.

Harmful to wood finishes and plastics.

When using this product

keep out of eyes.Do not inhale or ingest.

Stop use and ask a doctor if skin irritation develops.

Keep out of reach of children